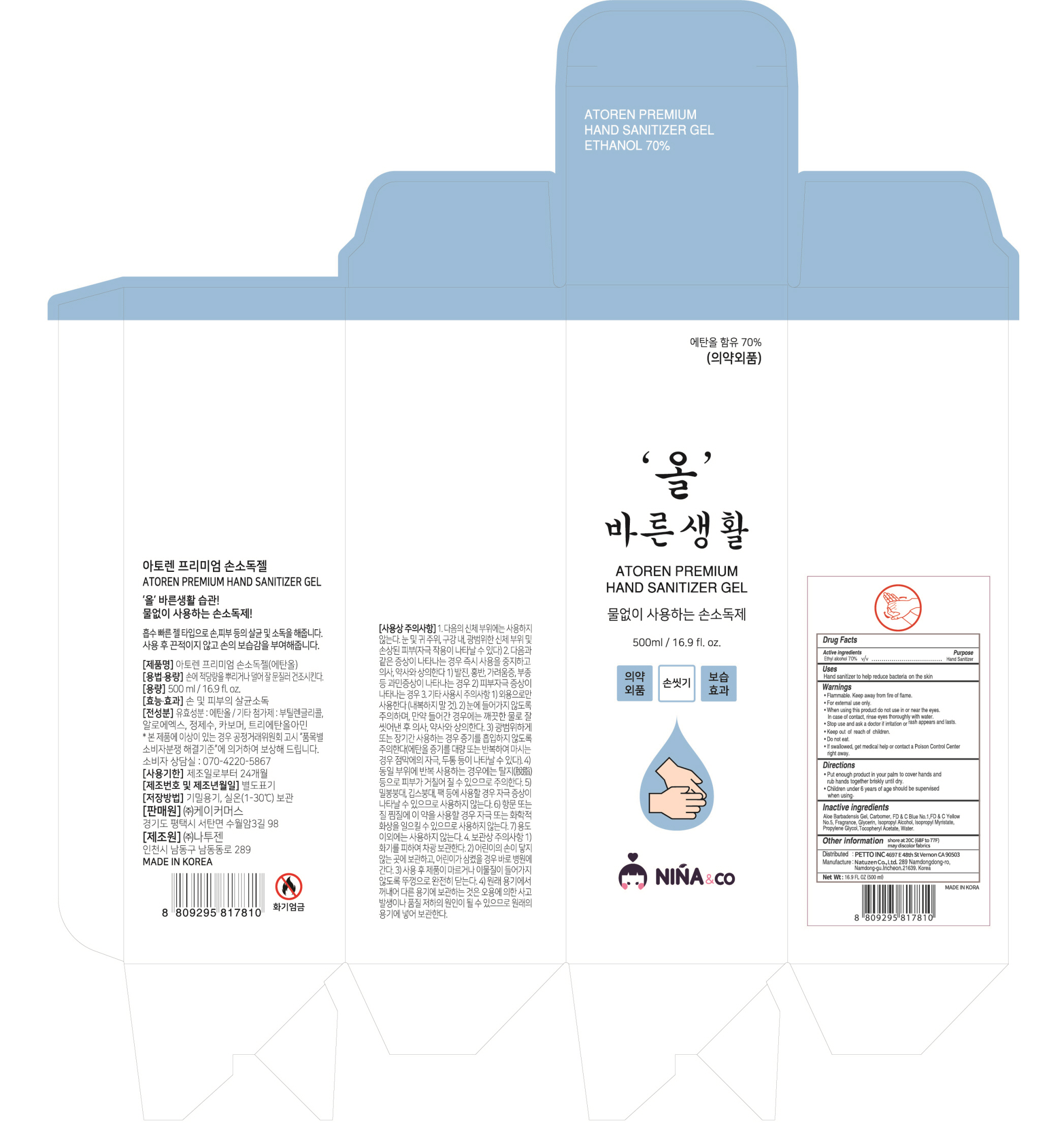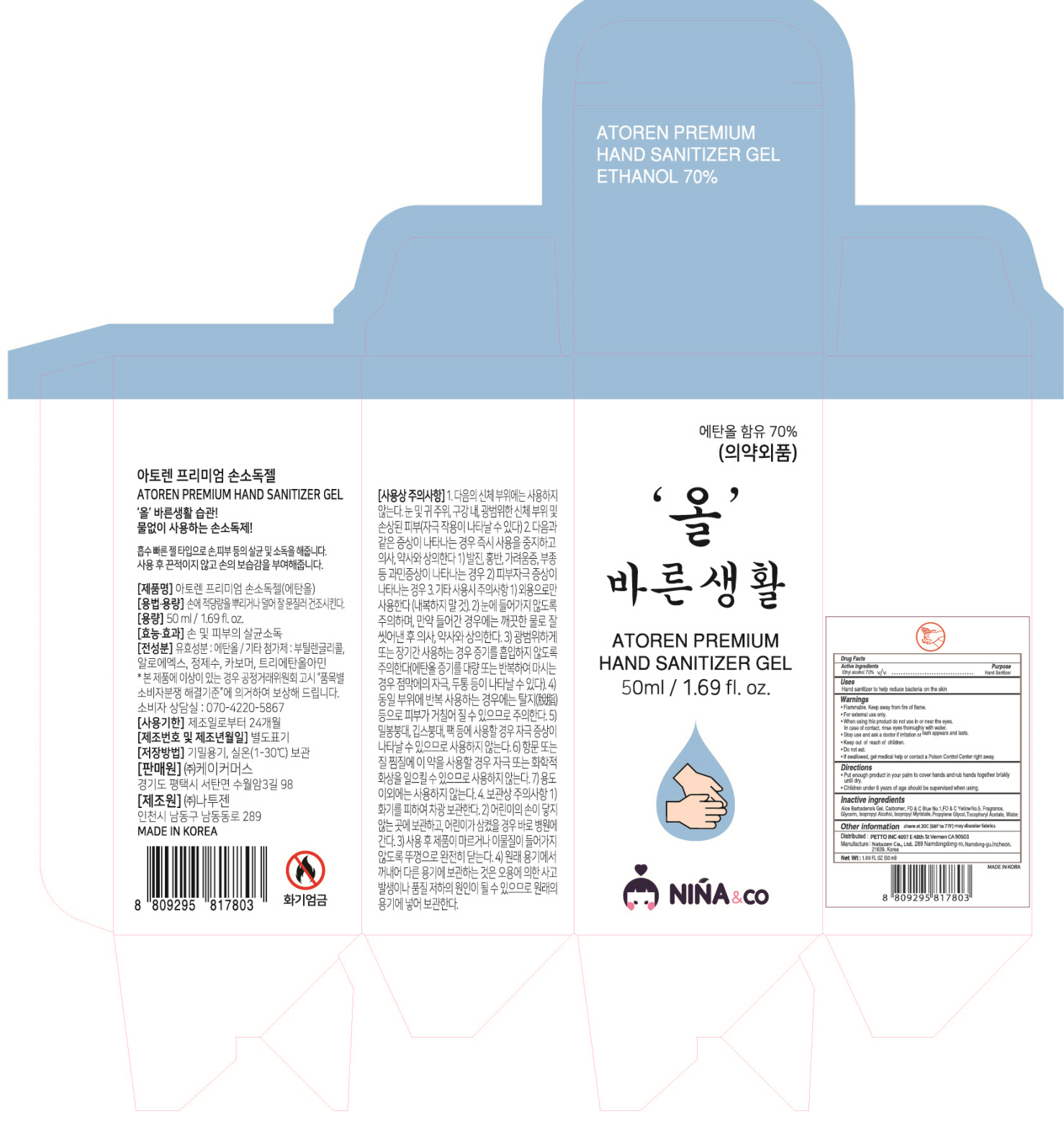 DRUG LABEL: ATOREN PREMIUM HAND SANITIZER
NDC: 74775-010 | Form: GEL
Manufacturer: Kcommerce Co.,Ltd
Category: otc | Type: HUMAN OTC DRUG LABEL
Date: 20200413

ACTIVE INGREDIENTS: ALCOHOL 70 g/100 mL
INACTIVE INGREDIENTS: Water; ALOE VERA LEAF; CARBOMER HOMOPOLYMER, UNSPECIFIED TYPE; GLYCERIN

ACTIVE INGREDIENT

Active ingredients: Ethyl alcohol 70% v/v

INACTIVE INGREDIENT

Inactive ingredients:

Aloe Barbadensis Gel, Carbomer, FD &C Blue No.1,FD &C Yellow No.5, Fragrance, Glycerin, Isopropyl Alcohol, Isopropyl Myristate,
Propylene Glycol, Tocopheryl Acetate, Water.

PURPOSE

Purpose: Hand Sanitizer

WARNINGS

• Flammable. Keep away from fire or flame.
• For external use only.
• When using this product do not use in or near the eyes.
In case of contact, rinse eyes thoroughly with water.
• Stop use and ask a doctor if irritation or rash appears and lasts.
• Keep Out of Reach of Children.
• Do not eat.
• If swallowed, get medical help or contact a Poison Control
Center right away

KEEP OUT OF REACH OF CHILDREN

Uses

Hand sanitizer to help reduce bacteria on the skin

Directions

• Put enough product in your palm to cover hands and rub hands together briskly until dry.
• Children under 6 years of age should be supervised when using. Not recommended for infants.